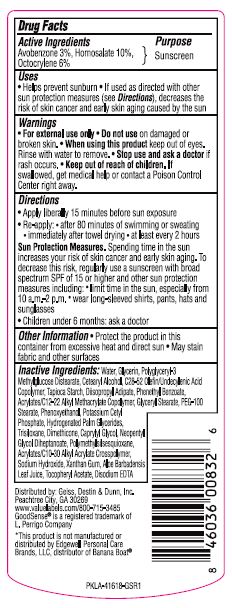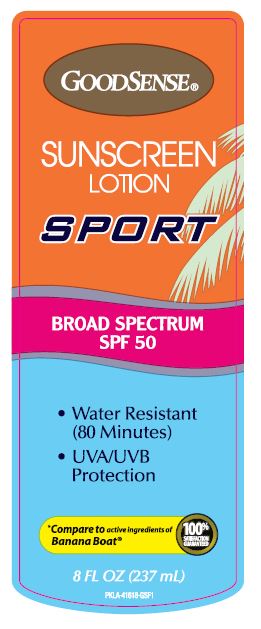 DRUG LABEL: GoodSense Sport Sunscreen SPF 50
NDC: 70281-632 | Form: LOTION
Manufacturer: Solskyn Personal Care, LLC
Category: otc | Type: HUMAN OTC DRUG LABEL
Date: 20190724

ACTIVE INGREDIENTS: HOMOSALATE 10 g/100 g; AVOBENZONE 3 g/100 g; OCTOCRYLENE 5 g/100 g
INACTIVE INGREDIENTS: POLYGLYCERYL-3 DIISOSTEARATE; CETOSTEARYL ALCOHOL; UNDECYLENIC ACID; DIISOPROPYL ADIPATE; SODIUM HYDROXIDE; GLYCERYL MONOSTEARATE; TRISILOXANE; PEG-100 STEARATE; POTASSIUM CETYL PHOSPHATE; NEOPENTYL GLYCOL DIHEPTANOATE; GLYCERIN; DIMETHICONE; CAPRYLYL GLYCOL; POLYMETHYLSILSESQUIOXANE (4.5 MICRONS); PHENETHYL BENZOATE; PHENOXYETHANOL; CARBOMER INTERPOLYMER TYPE A (55000 CPS); WATER; STARCH, TAPIOCA; HYDROGENATED PALM GLYCERIDES

GoodSense BB Sport Sunscreen SPF 50

Active Ingredients

Avobenzone 10%
Homosalate 3%
Octocrylene 5%

Purpose

Sunscreen

Uses

- Helps prevent sunburn.
- If used as directed with other sun protection measures (see Directions), decreases the risk of skin cancer and early skin aging caused by the sun

Warnings

For external use only

Do not use on damaged or broken skin

When using this product keep out of eyes. Rinse with water to remove.

Stop use and ask a doctor if rash occurs.

Keep out of reach of children. If swallowed, get medical help or contact a Poison Control Center right away.

Directions

- Apply liberally 15 minutes before sun exposure
- Re-apply after 80- minutes of swimming or sweating
- Immediately after towel drying
- At least every 2 hours

Sun Protection Measures.

Spending time in the sun increases your risk of skin cancer and early skin aging. To decrease this risk, regularly use a sunscreen with broad spectrum SPF of 15 or high and other sun protection measures including:

- Limit time in the sun, especially from 10a.m.-2 p.m.
- Wear long-sleeved shirts, pants, hats, and sunglasses.
- Children under 6 months: ask a doctor

Other Information

- Protect the product in this container from excessive heat and direct sun
- May stain fabric and other surfaces

Inactive Ingredients

Water, Glycerin, Polyglyceryl-3 Methylglucose Distearate, Cetearyl Alcohol, C28-52 Olefin/Undecylenic Acid Copolymer, Tapioca Starch, Dispropyl Adipate, Diheptanoate, Phenethyl Benzoate, Acrylates/C12-22 Alkyl Methacrylate Copolymer, Glyceryl Stearate, PEG-I00 Stearate, Phenoxyethanol, Potassium Cetyl Phosphate, Hydronated Palm Glycerides, Trisiloxane, Dimethicone, Caprylyl Glycol, Neopentyl Glycol Diheptanoate, Polymethylsilsesquioxane, Acrylates/C19-30 Alkyl Acrylate Crosspolymer, Sodium Hydroxide, Xanthan Gum, Aloe Barbadensis Leaf Juice, Tocopheryl Acetate, Disodium EDTA

Questions

Distributed by Geiss, Destin, & Dunn Inc., Peach tree City, GA 30269

www.valuelabels.com /800-715-3485

GoodSense® is a registered trademark of L. Perrigo Company

*This product is not manufactured or distributed by Edgewell Personal Care Brands, LLC, Distributor of Banana Boat®

Principal Display Panel

GOODSENSE®

SUNSCREEN

LOTION

SPORT

BROAD SPECTRUM

SPF 50

Water Resistant

(80 Minutes)

UVA/UVB

Protection

*Compare to active ingredients of Banana Boat®

100% Satisfaction Guaranteed

8 FL OZ (237 mL)